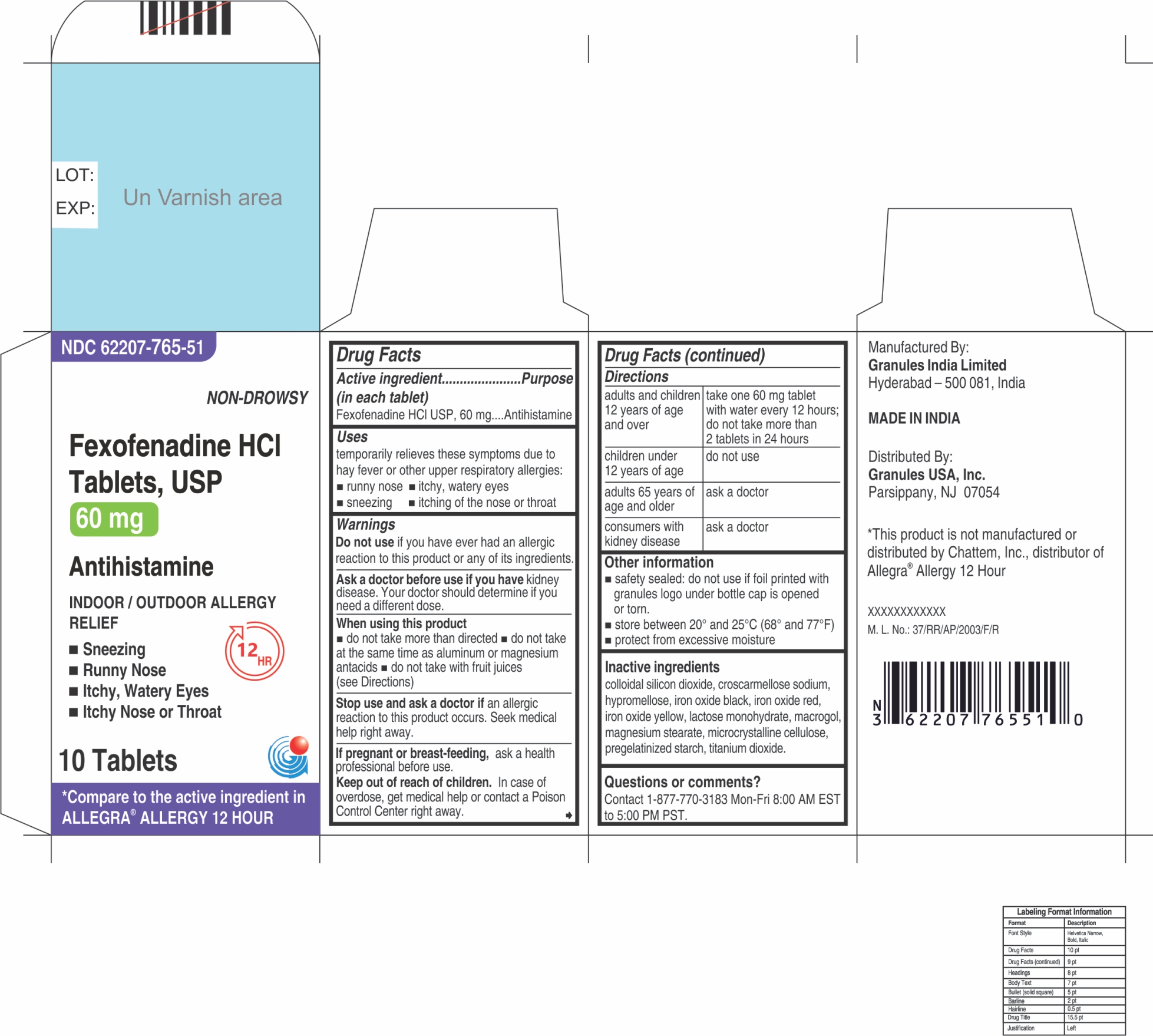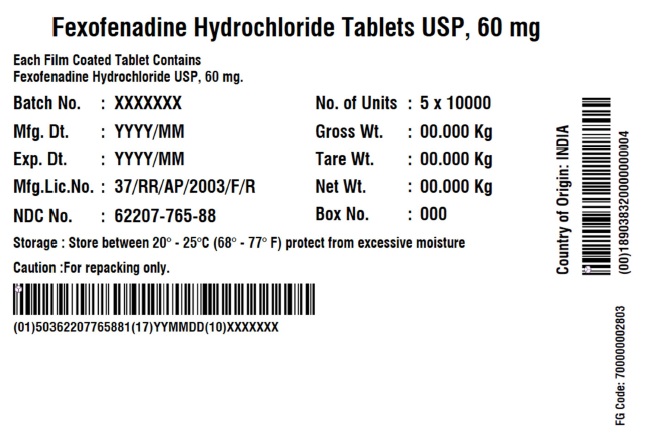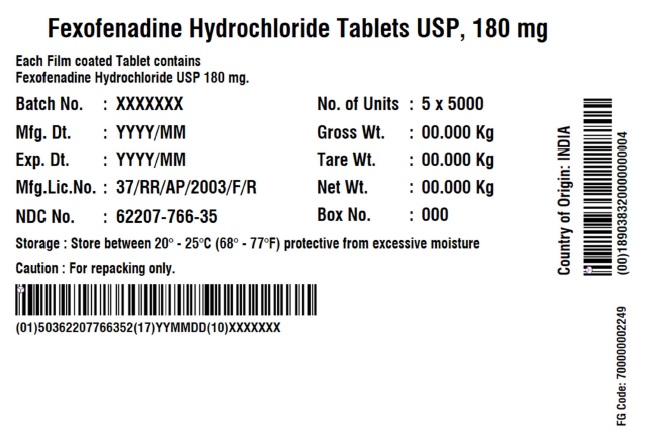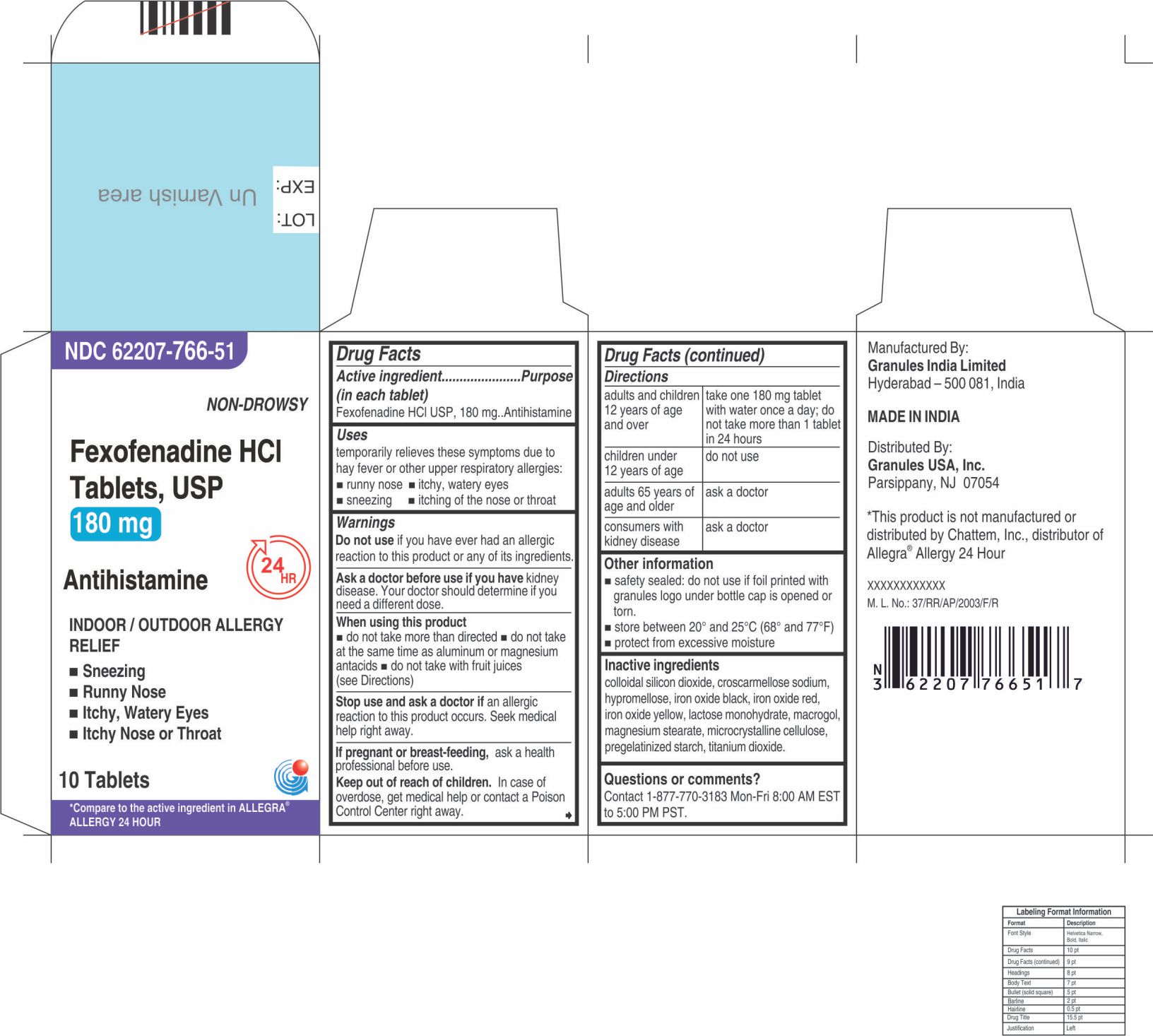 DRUG LABEL: Fexofenadine Hydrochloride
NDC: 62207-765 | Form: TABLET
Manufacturer: Granules India Ltd
Category: otc | Type: HUMAN OTC DRUG LABEL
Date: 20250805

ACTIVE INGREDIENTS: FEXOFENADINE HYDROCHLORIDE 60 mg/1 1
INACTIVE INGREDIENTS: CROSCARMELLOSE SODIUM; FERROSOFERRIC OXIDE; FERRIC OXIDE RED; FERRIC OXIDE YELLOW; HYPROMELLOSE 2910 (15 MPA.S); LACTOSE MONOHYDRATE; MAGNESIUM STEARATE; MICROCRYSTALLINE CELLULOSE; POLYETHYLENE GLYCOL 6000; SILICON DIOXIDE; STARCH, CORN; TITANIUM DIOXIDE

Fexofenadine HCl Tablets USP, 60 mg and 180 mg

ACTIVE INGREDIENT(S)

Fexofenadine HCl USP 60 mg (for 60 mg)
Fexofenadine HCl USP 180 mg (for 180 mg)

PURPOSE

Antihistamine

USE(S)

temporarily relieves these symptoms due to hay fever or other upper respiratory allergies:

- runny nose
- itchy, water eyes
- sneezing
- itching of the nose or throat

WARNINGS

Do not use
if you have ever had an allergic reaction to this product or any of its ingredients.
Ask a doctor before use if you have
kidney disease. Your doctor should determine if you need a different dose.
When using this product

- do not take more than directed
- do not take at the same time as aluminum or magnesium antacids
- do not take with fruit juices (see Directions)

Stop use and ask a doctor if
an allergic reaction to this product occurs. Seek medical help right away.
If pregnant or breast-feeding
ask a health professional before use.

Keep out of reach of children

In case of overdose, get medical help or contact a Poison Control Center right away.

DIRECTIONS

adults and children 12 years of age and over | take one 60 mg tablet with water every 12 hours; do not take more than 2 tablets in 24 hours (for 60 mg) take one 180 mg tablet with water once a day; do not take more than 1 tablet in 24 hours (for 180 mg)
children under 12 years of age | do not use
adults 65 years of age and older | ask a doctor
consumers with kidney disease | ask a doctor

OTHER INFORMATION

- Safety-sealed: do not use if foil printed with granules logo under bottle cap is opened or torn.
- Do not use if carton is opened or if individual blister units are torn or opened.
- store between 20º and 25ºC (68º and 77ºF)
- protect from excessive moisture

INACTIVE INGREDIENTS

colloidal silicon dioxide, croscarmellose sodium, hypromellose, iron oxide black, iron oxide red, iron oxide yellow, lactose monohydrate, macrogol, magnesium stearate, microcrystalline cellulose, pregelatinized starch, titanium dioxide.

QUESTIONS OR COMMENTS

Contact 1-877-770-3183 Mon-Fri 8:00 AM EST to 5:00 PM PST
Manufactured By:
Granules India Limited
Hyderabad-500 081, India
MADE IN INDIA
Distributed By:
Granules USA, Inc.
Parsippany, NJ 07054